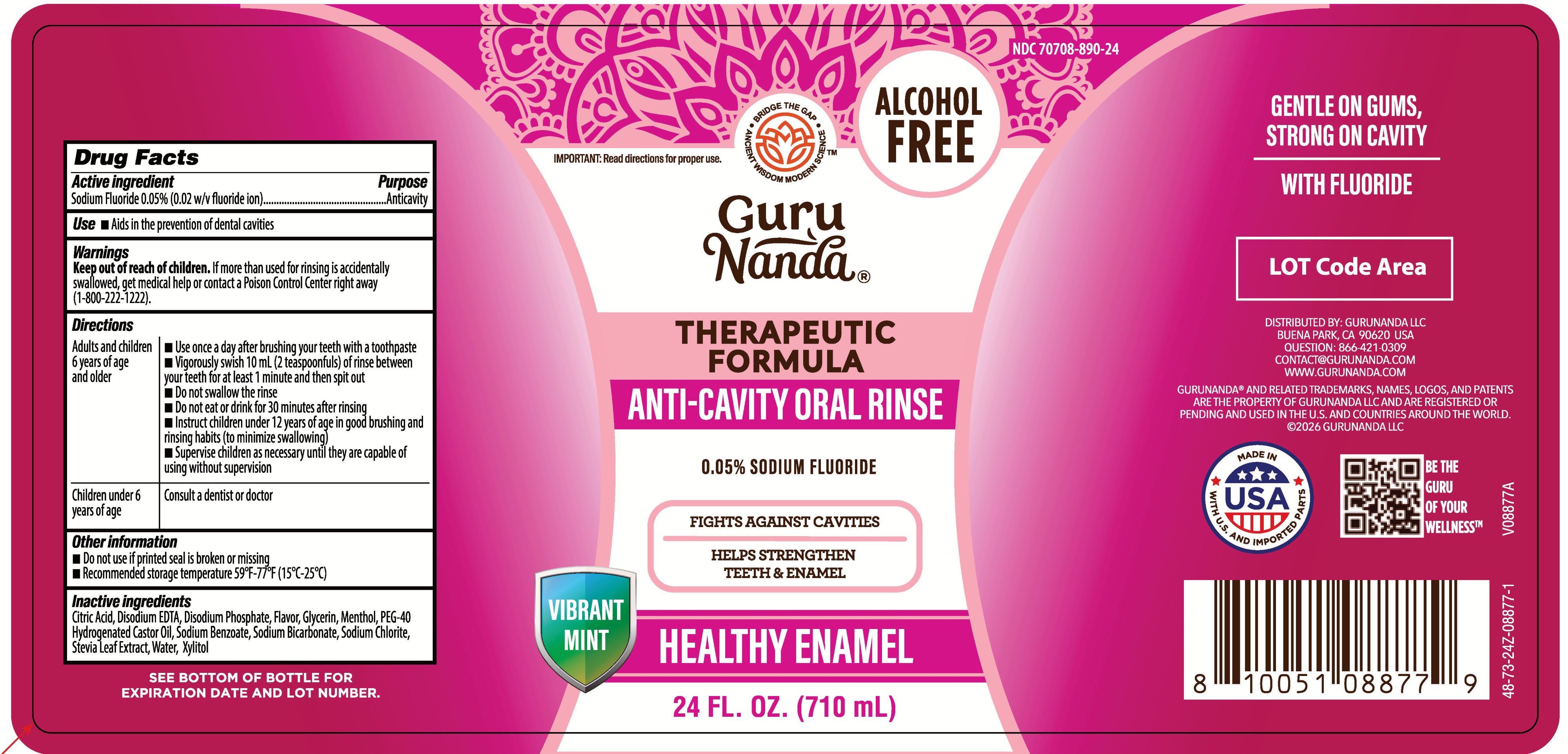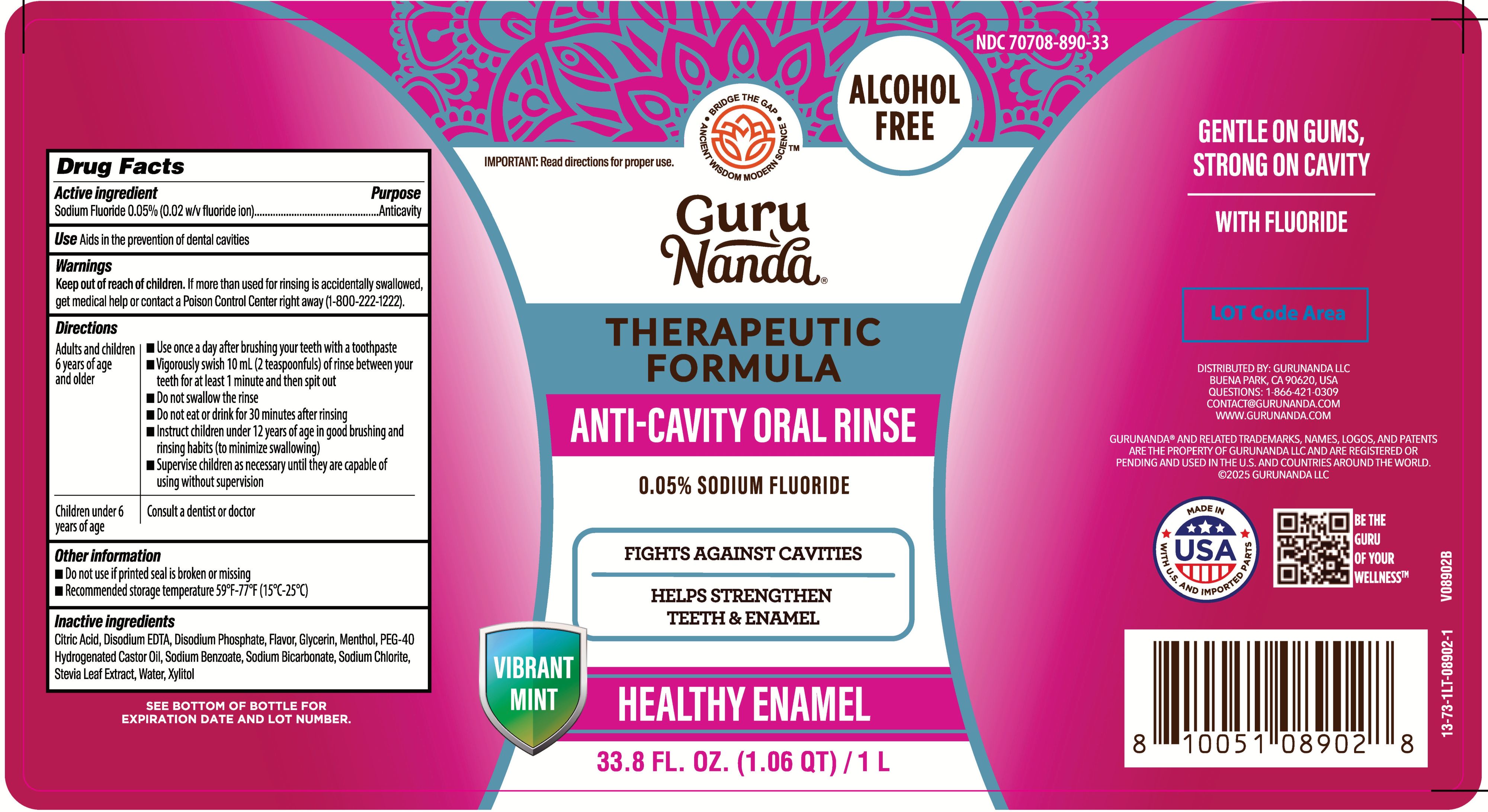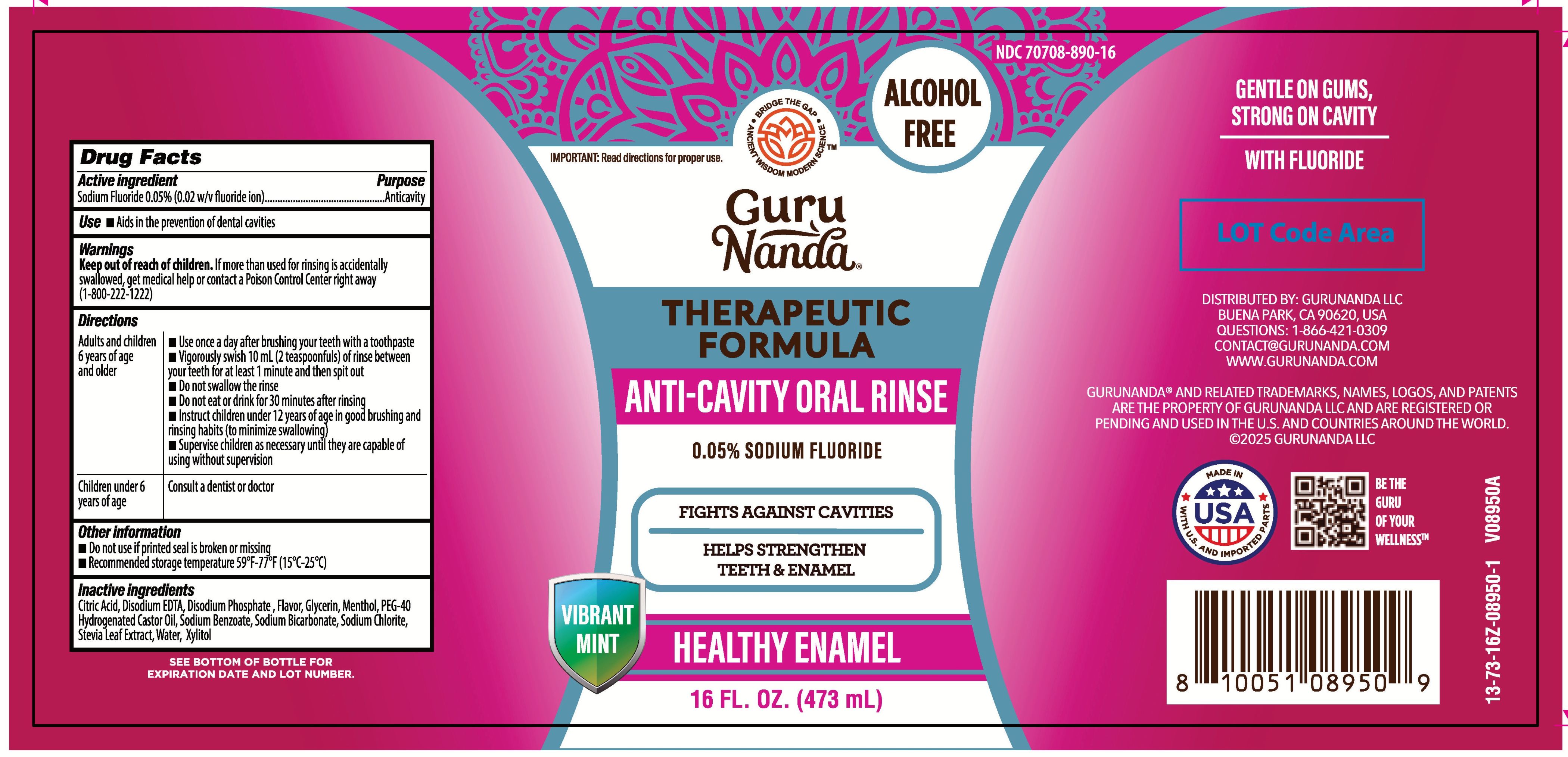 DRUG LABEL: GuruNanda Anti-Cavity
NDC: 70708-890 | Form: RINSE
Manufacturer: GURUNANDA, LLC
Category: otc | Type: HUMAN OTC DRUG LABEL
Date: 20260119

ACTIVE INGREDIENTS: SODIUM FLUORIDE 0.2 mg/1 mL
INACTIVE INGREDIENTS: GLYCERIN; SODIUM BENZOATE; DISODIUM PHOSPHATE; XYLITOL; SODIUM CHLORITE; EDETATE DISODIUM; PEG-40 HYDROGENATED CASTOR OIL; CITRIC ACID; STEVIA LEAF; LEVOMENTHOL; WATER; SODIUM BICARBONATE

GuruNanda Anti-Cavity Oral Rinse

Active ingredient

Sodium Fluoride 0.05% (0.2 w/v fluoride ion)

Purpose

Anticavity

Uses

Aids in the prevention of dental cavities

Warnings

Keep out of reach of children

If more than used for rinsing is accidentally swallowed, get medical help or contact a Poison Control Center right away (1-800-222-1222).

Directions

Adults and children 12 years of age and older:

- Use once a day after brushing your teeth with a toothpaste.
- Vigorously swish 10 mL of rinse between your teeth for 1 minute and then spit out.
- Do not swallow the rinse.
- Do not eat or drink for 30 minutes after rinsing.
- Instruct children under 12 years of age in good brushing and rinsing habits (to minimize swallowing).
- Supervise children as necessary until they are capable of using without supervison.

Children under 6 years of age:

- Consult a dentist or doctor

Other information

- Do not use if printed seal is broken or missing
- Recommended storage temperature 59°F-77°F (15°C-25°C)

Inactive ingredients

Water, Glycerin, PEG-40 Hydrogenated Castor Oil, Sodium Benzoate, Sodium Bicarbonate, Disodium Phosphate, Sodium Chlorite, Menthol, Stevia Leaf Extract, Flavor, Disodium EDTA, Xylitol, Citric Acid